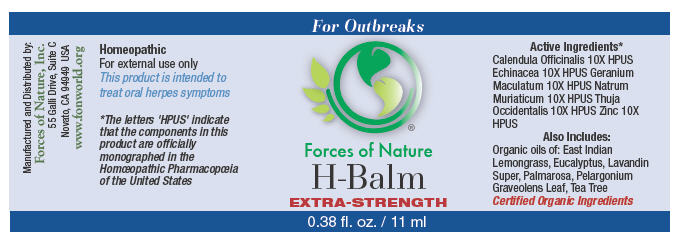 DRUG LABEL: H-Balm 
NDC: 51393-6557 | Form: SOLUTION/ DROPS
Manufacturer: Forces of Nature
Category: homeopathic | Type: HUMAN OTC DRUG LABEL
Date: 20100824

ACTIVE INGREDIENTS: CALENDULA OFFICINALIS FLOWERING TOP 10 [hp_X]/1000 mL; Geranium Maculatum Root 10 [hp_X]/1000 mL; SODIUM CHLORIDE 10 [hp_X]/1000 mL; THUJA OCCIDENTALIS LEAFY TWIG 10 [hp_X]/1000 mL; Zinc 10 [hp_X]/1000 mL; Echinacea angustifolia 10 [hp_X]/1000 mL

H-Balm Extra Strength

Drug Facts

Indications

For the treatment of oral herpes caused by herpes simplex 1 or 2 after diagnosis by a physician. Herpes is a contagious viral infection with symptoms of rashes or blisters, redness and pain.

ACTIVE INGREDIENT

PURPOSE

Homeopathic Active Ingredients [The letters 'HPUS' indicate that the components in this product are officially monographed in the Homœopathic Pharmacopœia of the United States.]
Equal parts of: | Purpose
Calendula Officinalis 10X HPUS | Promotes healthy skin and healing
Echinacea 10X HPUS | Relief from skin irritation
Geranium Maculatum 10X HPUS | Relief for skin ulcers
Natrum Muriaticum 10X HPUS | Relief for herpes, painful skin eruptions
Thuja Occidentalis 10X HPUS | Relief for herpes, skin eruptions, itching or burning pain
Zinc 10X HPUS | Support for immune function

INACTIVE INGREDIENT

Also Contains Certified Organic Oils:

East Indian Lemongrass, Lavandin Super, Pelargonium Graveolens Leaf Oil, Tea Tree, Palmarosa oil, Eucalyptus oil.

Directions

Apply 2-3 drops on moistened swab and dab to problem area 3-4 times per day during an outbreak. For best results use immediately and often at the very first signs of an outbreak or when you feel one coming on. Use of this product during the prodromal phase (tingling some experience before an outbreak) may improve results. Wash hands after use. Avoid contact with eyes.

Warnings

Viral infections are contagious, and this product will not prevent the spread of the virus that causes herpes or any other virus.

Some individuals may be sensitive to tea tree or other oils. Begin with a small drop to determine if the product causes any increased redness or irritation and discontinue use if it irritates your skin.

PREGNANCY OR BREAST FEEDING

If you are pregnant or breast-feeding, ask a health professional before use.

Keep out of the reach of children.

WHEN USING

If accidental ingestion of more than several drops, get medical help or contact a Poison Control Center.

STOP USE

For external use only. Avoid contact with eyes. Stop use and ask a doctor if condition worsens or symptoms last more than 7 days.

Manufactured by:
Forces of Nature, Inc.
55 Galli Drive, Suite C
Novato, CA 94949 USA
www.fonworld.org

Product questions?

877-975-3797

NDC #: 51393-6557-1 (11ml) // 51393-6557-2 (33ml)

Principal Display Panel - 11 ml Bottle Label

For Outbreaks

Forces of Nature

H-Balm

EXTRA STRENGTH

0.38 fl. oz. / 11 ml